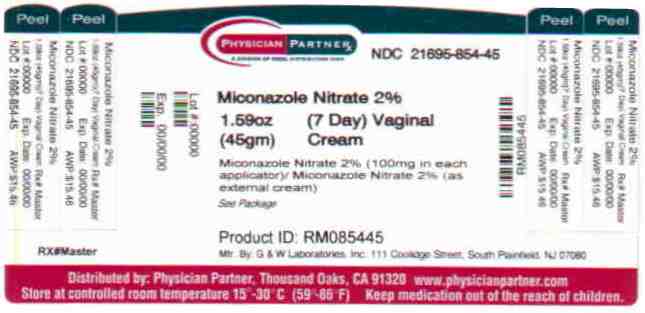 DRUG LABEL: Miconazole Nitrate
NDC: 21695-854 | Form: CREAM
Manufacturer: Rebel Distributors Corp
Category: otc | Type: HUMAN OTC DRUG LABEL
Date: 20110217

ACTIVE INGREDIENTS: MICONAZOLE NITRATE 20 mg/1 g
INACTIVE INGREDIENTS: BENZOIC ACID; BUTYLATED HYDROXYANISOLE; MINERAL OIL; WATER

Miconazole Nitrate 2% Drug Facts

Active ingredient

Miconazole Nitrate 2% (100 mg in each applicator)

Purpose

Vaginal antifungal

Keep Out of Reach of Children

If swallowed, get medical help or contact a
Poison Control Center right away.

Uses

. treats repeat vaginal yeast infections
. relieves external itching and irritation due to a repeat vaginal yeast infection

Warnings

For vaginal use only
Ask a doctor before use if you have
. never had a vaginal yeast infection diagnosed by a doctor
. 1 or more of the following:
abdominal pain, fever, chills, nausea, vomiting, foul-smelling vaginal discharge
. vaginal yeast infections often (such as once a month or 3 in 6 months)
. been exposed to the human immunodeficiency virus (HIV) that causes AIDS
Ask a doctor or pharmacist before use if you are taking the prescription
blood thinning medication warfarin, because bleeding or bruising may occur.
When using this product
. do not use tampons, douches, spermicides, or other vaginal products
. do not have vaginal intercourse
. condoms and diaphragms may be damaged and fail to prevent pregnancy or sexually transmitted diseases (STDs)
Stop use and ask a doctor if
. symptoms do not get better in 3 days
. symptoms last more than 7 days
. you get abdominal pain, fever, chills, nausea, vomiting, foul-smelling vaginal discharge, or rash
If pregnant or breast-feeding, ask a health professional before use.

Other Information

. do not purchase if printed "Safety Sealed" carton
overwrap is broken or missing
. do not use if seal over tube opening has been punctured or cannot be seen
. store at room temperature 15°-30°C (59°-86°F), avoid heat over 30°C or 86°F.

Directions

. before using this product read the enclosed consumer
information leaflet for complete instructions
. adults and children 12 years of age and over:
. applicator: insert one applicatorful into the vagina at bedtime for 7 nights in a row
. external cream: squeeze a small amount of cream onto your fingertip.
Gently apply the cream onto the itchy, irritated skin outside the
vagina. Use daily for up to 7 days as needed
. children under 12 years of age: ask a doctor

Inactive ingredients

benzoic acid, BHA, mineral oil, peglicol 5 oleate,
pegoxol 7 stearate, purified water